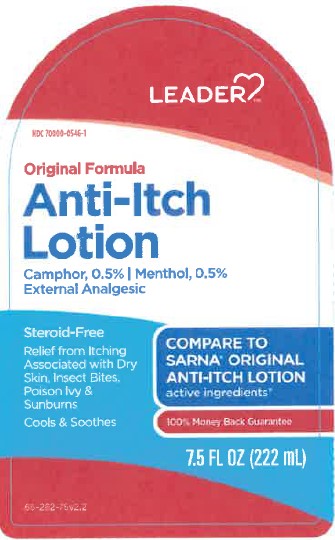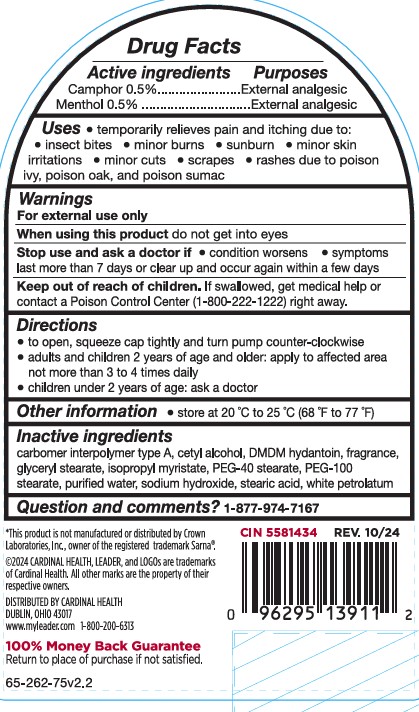 DRUG LABEL: Leader Anti-Itch
NDC: 70000-0546 | Form: LOTION
Manufacturer: LEADER/Cardinal Helath 110, Inc.
Category: otc | Type: HUMAN OTC DRUG LABEL
Date: 20251119

ACTIVE INGREDIENTS: CAMPHOR (SYNTHETIC) 0.5 g/100 g; MENTHOL 0.5 g/100 g
INACTIVE INGREDIENTS: CARBOMER INTERPOLYMER TYPE A (55000 CPS); ISOPROPYL MYRISTATE; WATER; PEG-40 STEARATE; CETYL ALCOHOL; PEG-100 STEARATE; STEARIC ACID; DMDM HYDANTOIN; SODIUM HYDROXIDE; PETROLATUM; GLYCERYL STEARATE SE

Leader Original Anti Itch Lotion

ACTIVE INGREDIENT

Camphor 0.5%

Menthol 0.5%

INDICATIONS AND USAGE

temporary relieves pain and itching due to:

insect bites

minor burns

sunburn

minor skin irritations

minor cuts

scrapes

rashes due to poison ivy, poison oak, and poison sumac

WARNINGS

For external use only

ASK DOCTOR

on chicken pox

on measles

WHEN USING

do not get into eyes

STOP USE

condition worsens

symptoms last more than 7 days or clear up and occur again within a few days

KEEP OUT OF REACH OF CHILDREN

If swallowed, get medical help or contact a Poison Control Center right away.

PURPOSE

Anti-itch

External Analgesic

Directions

to open, squeeze cap tightly and turn pump counter-clockwise

adults and children 2 years and older: apply to affected area not more than 3 to 4 times daily

children under 2 years: ask a doctor

Other information

store at 20 °C to 25 °C (68 °F to 77 °F)

INACTIVE INGREDIENT

carbomer interpolymer type A, cetyl alcohol, DMDM hydantoin, fragrance, glyceryl
stearate, isopropyl myristate, PEG-40 stearate, PEG-100 stearate,
purified water, sodium hydroxide, stearic acid, white petrolatum

RECENT MAJOR CHANGES

Update to version number to the most recent label with updated inactive ingredient list

Updated Titles to remove repeats of Section Type

PACKAGE LABEL

Compare to Sarna Original Anti-Itch lotion

Original Formula Anti-Itch Lotion

Camphor 0.5%

Menthol 0.5%

Steroid Free

Relief from itching associated with dry skin, insectr bites, poison ivy and Sunburn

Cools and Soothes